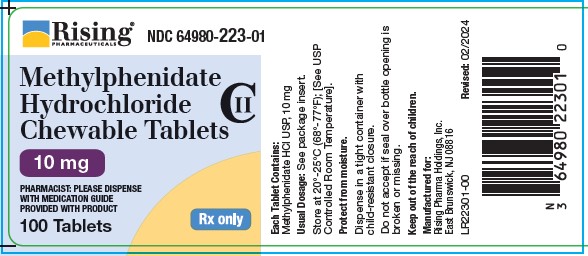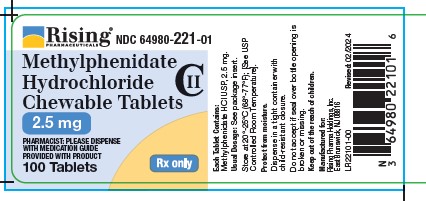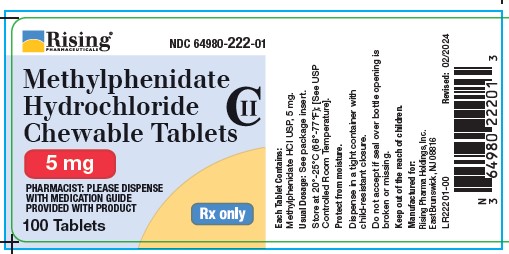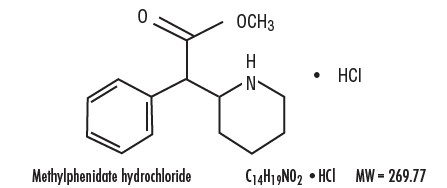 DRUG LABEL: Methylphenidate Hydrochloride
NDC: 64980-221 | Form: TABLET, CHEWABLE
Manufacturer: Rising Pharma Holdings, Inc.
Category: prescription | Type: HUMAN PRESCRIPTION DRUG LABEL
Date: 20250312
DEA Schedule: CII

ACTIVE INGREDIENTS: METHYLPHENIDATE HYDROCHLORIDE 2.5 mg/1 1
INACTIVE INGREDIENTS: CELLULOSE, MICROCRYSTALLINE; GUAR GUM; MALTOSE; STEARIC ACID; SUCRALOSE

HIGHLIGHTS OF PRESCRIBING INFORMATION

These highlights do not include all the information needed to use METHYLPHENIDATE HYDROCHLORIDE Chewable Tablets safely and effectively. See full prescribing information for METHYLPHENIDATE HYDROCHLORIDE Chewable Tablets. METHYLPHENIDATE HYDROCHLORIDE Chewable Tablets (Methylphenidate hydrochloride), for oral use, CII
Initial U.S. Approval: 1955

WARNING: ABUSE, MISUSE, AND ADDICTION

See full prescribing information for complete boxed warning.

Methylphenidate hydrochloride has a high potential for abuse and misuse, which can lead to the development of a substance use disorder, including addiction. Misuse and abuse of CNS stimulants, including methylphenidate hydrochloride, can result in overdose and death (5.1, 9.2, 10):

- Before prescribing methylphenidate hydrochloride, assess each patient’s risk for abuse, misuse, and addiction.
- Educate patients and their families about these risks, proper storage of the drug, and proper disposal of any unused drug.
- Throughout treatment, reassess each patient’s risk and frequently monitor for signs and symptoms of abuse, misuse, and addiction.

1 INDICATIONS AND USAGE

Methylphenidate Hydrochloride Chewable Tablets are a central nervous system (CNS) stimulant indicated for the treatment of:

- Attention Deficit Hyperactivity Disorder (ADHD) in patients 6 years of age and older (1)
- Narcolepsy (1)

2 DOSAGE AND ADMINISTRATION

- Pediatric Patients 6 Years and Older: Start with 5 mg twice daily (before breakfast and lunch); titrate the dose in weekly increments of 5 mg to 10 mg. Daily dosages above 60 mg are not recommended. (2.2)
- Adults: Administer in divided doses 2 or 3 times daily, preferably 30 to 45 minutes before meals. Maximum recommended daily dosage is 60 mg. (2.2)
- Administer with at least 8 ounces (a full glass) of water or other fluid. (2.2)

3 DOSAGE FORMS AND STRENGTHS

Chewable tablets: 2.5 mg, 5 mg, and 10 mg.

4 CONTRAINDICATIONS

- Known hypersensitivity to methylphenidate or other components of methylphenidate hydrochloride chewable tablets (4)
- Concurrent treatment with a monoamine oxidase inhibitor (MAOI), or use of an MAOI within the preceding 14 days (4)

5 WARNINGS AND PRECAUTIONS

- Risks to Patients with Serious Cardiac Disease: Avoid use in patients with known structural cardiac abnormalities, cardiomyopathy, serious cardiac arrhythmias, coronary artery disease, or other serious cardiac disease. (5.2)
- Increased Blood Pressure and Heart Rate: Monitor blood pressure and pulse. (5.3)
- Psychiatric Adverse Reactions: Prior to initiating methylphenidate hydrochloride, screen patients for risk factors for developing a manic episode. If new psychotic or manic symptoms occur, consider discontinuing methylphenidate hydrochloride. (5.4)
- Priapism: If abnormally sustained or frequent and painful erections occur, patients should seek immediate medical attention. (5.5)
- Peripheral Vasculopathy, including Raynaud’s Phenomenon: Careful observation for digital changes is necessary during methylphenidate hydrochloride treatment. Further clinical evaluation (e.g., rheumatology referral) may be appropriate for patients who develop signs or symptoms of peripheral vasculopathy. (5.6)
- Long-Term Suppression of Growth in Pediatric Patients: Closely monitor growth (height and weight) in pediatric patients. Pediatric patients not growing or gaining height or weight as expected may need to have their treatment interrupted. (5.7)
- Acute Angle Closure Glaucoma: methylphenidate hydrochloride-treated patients considered at risk for acute angle closure glaucoma (e.g., patients with significant hyperopia) should be evaluated by an ophthalmologist. (5.8)
- Increased Intraocular Pressure (IOP) and Glaucoma: Prescribe methylphenidate hydrochloride to patients with open-angle glaucoma or abnormally increased IOP only if the benefit of treatment is considered to outweigh the risk. Closely monitor patients with a history of increased IOP or open-angle glaucoma. (5.9)
- Motor and Verbal Tics, and Worsening of Tourette’s Syndrome: Before initiating methylphenidate hydrochloride, assess the family history and clinically evaluate patients for tics or Tourette’s syndrome. Regularly monitor patients for the emergence or worsening of tics or Tourette’s syndrome. Discontinue treatment if clinically appropriate. (5.10)
- Risk of Choking: Taking this product without enough liquid may cause choking. Discontinue Methylphenidate Hydrochloride Chewable Tablets and seek immediate medical attention if chest pain, vomiting, difficulty in swallowing, or difficulty in breathing occur after administration. (5.11)

6 ADVERSE REACTIONS

Common adverse reactions: tachycardia, palpitations, headache, insomnia, anxiety, hyperhidrosis, weight loss, decreased appetite, dry mouth, nausea, and abdominal pain. (6)

To report SUSPECTED ADVERSE REACTIONS, contact Rising Pharma Holdings, Inc. at 1-844-874-7464 or FDA at 1-800-FDA-1088 or www.fda.gov/medwatch.

7 DRUG INTERACTIONS

- Antihypertensive Drugs: Monitor blood pressure. Adjust dosage of antihypertensive drug as needed. (7.1)

FULL PRESCRIBING INFORMATION

WARNING: ABUSE, MISUSE, AND ADDICTION

Methylphenidate hydrochloride has a high potential for abuse and misuse, which can lead to the development of a substance use disorder, including addiction. Misuse and abuse of CNS stimulants, including methylphenidate hydrochloride, can result in overdose and death [see Overdosage (10)], and this risk is increased with higher doses or unapproved methods of administration, such as snorting or injection.

Before prescribing methylphenidate hydrochloride, assess each patient’s risk for abuse, misuse, and addiction. Educate patients and their families about these risks, proper storage of the drug, and proper disposal of any unused drug. Throughout methylphenidate hydrochloride treatment, reassess each patient’s risk of abuse, misuse, and addiction and frequently monitor for signs and symptoms of abuse, misuse, and addiction [see Warnings and Precautions (5.1) and Drug Abuse and Dependence (9.2)].

1 INDICATIONS AND USAGE

Methylphenidate Hydrochloride Chewable Tablets is indicated for the treatment of:

- Attention Deficit Hyperactivity Disorder (ADHD) in patients 6 years of age and older
- Narcolepsy

2 DOSAGE AND ADMINISTRATION

2.1 Pretreatment Screening

Prior to treating patients with Methylphenidate Hydrochloride Chewable Tablets, assess:

- for the presence of cardiac disease (i.e., perform a careful history, family history of sudden death or ventricular arrhythmia, and physical exam) [see Warnings and Precautions (5.2)].
- the family history and clinically evaluate patients for motor or verbal tics or Tourette’s syndrome before initiating Methylphenidate Hydrochloride Chewable Tablets [see Warnings and Precautions (5.10)].

2.2 Recommended Dosage and Administration Information

Pediatric Patients 6 years and Older
The recommended starting dosage is 5 mg orally twice daily before breakfast and lunch (preferably 30 to 45 minutes before meals). Increase the dosage gradually, in increments of 5 mg to 10 mg weekly. Daily dosage above 60 mg is not recommended.

Adults
Administer orally in divided doses 2 or 3 times daily, preferably 30 to 45 minutes before meals. The maximum recommended dosage is 60 mg daily. The average dosage is 20 to 30 mg daily. For adult patients who are unable to sleep if medication is taken late in the day, administer the last dose before 6 p.m.

Administer Methylphenidate Hydrochloride Chewable Tablets with at least 8 ounces (a full glass) of water or other fluid. Do not swallow whole. Taking this product without enough liquid may cause choking [see Warnings and Precautions (5.11)]

2.3 Dosage Reduction and Discontinuation

If paradoxical aggravation of symptoms or other adverse reactions occur, reduce dosage, or, if necessary, discontinue Methylphenidate Hydrochloride Chewable Tablets. If improvement is not observed after appropriate dosage adjustment over a one-month period, discontinue Methylphenidate Hydrochloride Chewable Tablets.

3 DOSAGE FORMS AND STRENGTHS

Chewable tablets:

- Each Methylphenidate Hydrochloride Chewable Tablet 2.5 mg is available as a white to off-white colored, grape flavored, rounded square shaped tablet with a convex surface, debossed with “τ” above “CHEW” on one side and “2.5” on the other side.
- Each Methylphenidate Hydrochloride Chewable Tablet 5 mg is available as a white to off-white colored, grape flavored, rounded square shaped tablet with a convex surface, debossed with “τ” above “CHEW” on one side and “5” on the other side.
- Each Methylphenidate Hydrochloride Chewable Tablet 10 mg is available as a white to off-white colored, grape flavored, scored rounded square shaped tablet with a convex surface, debossed with “τ” bisect “CHEW” on one side and “10” on the other side.

4 CONTRAINDICATIONS

Methylphenidate Hydrochloride Chewable Tablets is contraindicated in patients:

- with a known hypersensitivity to methylphenidate or other components of Methylphenidate Hydrochloride Chewable Tablets. Hypersensitivity reactions such as angioedema and anaphylactic reactions have been reported in patients treated with methylphenidate [see Adverse Reactions (6)].
- receiving concomitant treatment with monoamine oxidase inhibitors (MAOIs), and also within 14 days following discontinuation of treatment with a MAOI, because of the risk of hypertensive crisis [see Drug Interactions (7.1)].

5 WARNINGS AND PRECAUTIONS

5.1 Abuse, Misuse, and Addiction

Methylphenidate hydrochloride has a high potential for abuse and misuse. The use of methylphenidate hydrochloride exposes individuals to the risks of abuse and misuse, which can lead to the development of a substance use disorder, including addiction. methylphenidate hydrochloride can be diverted for non-medical use into illicit channels or distribution [see Drug Abuse and Dependence (9.2, 9.3)]. Misuse and abuse of CNS stimulants, including methylphenidate hydrochloride, can result in overdose and death [see Overdosage (10)], and this risk is increased with higher doses or unapproved methods of administration, such as snorting or injection.

Before prescribing methylphenidate hydrochloride, assess each patient’s risk for abuse, misuse, and addiction. Educate patients and their families about these risks and proper disposal of any unused drug. Advise patients to store methylphenidate hydrochloride chewable tablets in a safe place, preferably locked, and instruct patients to not give methylphenidate hydrochloride to anyone else. Throughout methylphenidate hydrochloride treatment, reassess each patient’s risk of abuse, misuse, and addiction and frequently monitor for signs and symptoms of abuse, misuse, and addiction.

5.2 Risks to Patients with Serious Cardiac Disease

Sudden death has been reported in patients with structural cardiac abnormalities or other serious cardiac disease who were taking CNS stimulants at the recommended ADHD dosage.

Avoid methylphenidate hydrochloride use in patients with known structural cardiac abnormalities, cardiomyopathy, serious cardiac arrhythmia, coronary artery disease, or other serious cardiac disease.

5.3 Increased Blood Pressure and Heart Rate

CNS stimulants cause an increase in blood pressure (mean increase approximately 2 to 4 mmHg) and heart rate (mean increase approximately 3 to 6 bpm). Some patients may have larger increases.

Monitor all methylphenidate hydrochloride-treated patients for hypertension and tachycardia.

5.4 Psychiatric Adverse Reactions

Exacerbation of Pre-Existing Psychosis

CNS stimulants may exacerbate symptoms of behavior disturbance and thought disorder in patients with a pre-existing psychotic disorder.

Induction of a Manic Episode in Patients with Bipolar Disorder

CNS stimulants may induce a manic or mixed episode in patients. Prior to initiating methylphenidate hydrochloride treatment, screen patients for risk factors for developing a manic episode (e.g., comorbid or history of depressive symptoms or a family history of suicide, bipolar disorder, and depression).

New Psychotic or Manic Symptoms

CNS stimulants, at the recommended dosage, may cause psychotic or manic symptoms (e.g., hallucinations, delusional thinking, or mania) in patients without a prior history of psychotic illness or mania. In a pooled analysis of multiple short-term, placebo-controlled studies of CNS stimulants, psychotic or manic symptoms occurred in approximately 0.1% of CNS stimulant-treated patients compared to 0% of placebo-treated patients. If such symptoms occur, consider discontinuing methylphenidate hydrochloride.

5.5 Priapism

Prolonged and painful erections, sometimes requiring surgical intervention, have been reported with methylphenidate use in both adult and pediatric male patients. Although priapism was not reported with methylphenidate initiation, it developed after some time on methylphenidate, often subsequent to an increase in dosage. Priapism also occurred during a methylphenidate withdrawal (drug holidays or during discontinuation).

Methylphenidate hydrochloride-treated patients who develop abnormally sustained or frequent and painful erections should seek immediate medical attention.

5.6 Peripheral Vasculopathy, including Raynaud’s Phenomenon

CNS stimulants, such as methylphenidate hydrochloride, used to treat ADHD are associated with peripheral vasculopathy, including Raynaud’s phenomenon. Signs and symptoms are usually intermittent and mild; however, sequelae have included digital ulceration and/or soft tissue breakdown. Effects of peripheral vasculopathy, including Raynaud’s phenomenon, were observed in postmarketing reports and at the therapeutic dosages of CNS stimulants in all age groups throughout the course of treatment. Signs and symptoms generally improved after reduction or discontinuation of the CNS stimulant.

Careful observation for digital changes is necessary during methylphenidate hydrochloride treatment. Further clinical evaluation (e.g., rheumatology referral) may be appropriate for methylphenidate hydrochloride-treated patients who develop signs or symptoms of peripheral vasculopathy.

5.7 Long-Term Suppression of Growth in Pediatric Patients

CNS stimulants have been associated with weight loss and slowing of growth rate in pediatric patients.

Careful follow-up of weight and height in pediatric patients ages 7 to 10 years who were randomized to either methylphenidate or non-medication treatment groups over 14 months, as well as in naturalistic subgroups of newly methylphenidate-treated and non-medication treated pediatric patients over 36 months (to the ages of 10 to 13 years), suggests that pediatric patients who received methylphenidate for 7 days per week throughout the year had a temporary slowing in growth rate (on average, a total of about 2 cm less growth in height and 2.7 kg less growth in weight over 3 years), without evidence of growth rebound during this development period.

Closely monitor growth (weight and height) in methylphenidate hydrochloride-treated pediatric patients. Pediatric patients who are not growing or gaining height or weight as expected may need to have their treatment interrupted.

5.8 Acute Angle Closure Glaucoma

There have been reports of angle closure glaucoma associated with methylphenidate treatment. Although the mechanism is not clear, methylphenidate hydrochloride-treated patients considered at risk for acute angle closure glaucoma (e.g., patients with significant hyperopia) should be evaluated by an ophthalmologist.

5.9 Increased Intraocular Pressure and Glaucoma

There have been reports of an elevation of intraocular pressure (IOP) associated with methylphenidate treatment [see Adverse Reactions (6)].

Prescribe methylphenidate hydrochloride to patients with open-angle glaucoma or abnormally increased IOP only if the benefit of treatment is considered to outweigh the risk. Closely monitor methylphenidate hydrochloride-treated patients with a history of abnormally increased IOP or open-angle glaucoma.

5.10 Motor and Verbal Tics, and Worsening of Tourette’s Syndrome

CNS stimulants, including methylphenidate, have been associated with the onset or exacerbation of motor and verbal tics. Worsening of Tourette’s syndrome has also been reported [see Adverse Reactions (6)].

Before initiating methylphenidate hydrochloride, assess the family history and clinically evaluate patients for tics or Tourette’s syndrome. Regularly monitor methylphenidate hydrochloride-treated patients for the emergence or worsening of tics or Tourette’s syndrome, and discontinue treatment if clinically appropriate.

5.11 Risk of Choking

Methylphenidate Hydrochloride Chewable Tablets may swell and block the throat or esophagus which can cause the patient to choke. Avoid use of Methylphenidate Hydrochloride Chewable Tablets in patients who have difficulty swallowing. Administer with at least 8 ounces of fluid [see Dosage and Administration (2.2)]. Discontinue Methylphenidate Hydrochloride Chewable Tablets and seek immediate medical attention if chest pain, vomiting, difficulty in swallowing, or difficulty in breathing occur after administration.

6 ADVERSE REACTIONS

The following are discussed in more detail in other sections of the labeling:

- Abuse, Misuse, and Addiction [see Boxed Warning, Warnings and Precautions (5.1), Drug Abuse and Dependence (9.2, 9.3)]
- Known hypersensitivity to methylphenidate or other ingredients of methylphenidate hydrochloride chewable tablets [see Contraindications (4)]
- Hypertensive crisis when used concomitantly with monoamine oxidase inhibitors [see Contraindications (4), Drug Interactions (7)]
- Risks to Patients with Serious Cardiac Disease [see Warnings and Precautions (5.2)]
- Increased Blood Pressure and Heart Rate [see Warnings and Precautions (5.3)]
- Psychiatric Adverse Reactions [see Warnings and Precautions (5.4)]
- Priapism [see Warnings and Precautions (5.5)]
- Peripheral Vasculopathy, including Raynaud’s Phenomenon [see Warnings and Precautions (5.6)]
- Long-Term Suppression of Growth in Pediatric Patients [see Warnings and Precautions (5.7)]
- Acute Angle Closure Glaucoma [see Warnings and Precautions (5.8)]
- Increased Intraocular Pressure and Glaucoma [see Warnings and Precautions (5.9)]
- Motor and Verbal Tics, and Worsening of Tourette’s Syndrome [see Warnings and Precautions (5.10)]
- Risk of Choking [see Warnings and Precautions (5.11)]

The following adverse reactions associated with the use of methylphenidate containing products were identified in other clinical studies, postmarketing reports, or literature. Because some of these reactions were reported voluntarily from a population of uncertain size, it is not always possible to reliably estimate their frequency or establish a causal relationship to drug exposure.

Infections and infestations: nasopharyngitis

Blood and the lymphatic system disorders: leukopenia, thrombocytopenia, anemia, pancytopenia

Immune system disorders: hypersensitivity reactions, including angioedema and anaphylaxis, auricular swelling, bullous conditions, eruptions, exanthemas

Metabolism and nutrition disorders: decreased appetite, reduced weight gain and suppression of growth during prolonged use in pediatric patients

Psychiatric disorders: insomnia, anxiety, restlessness, agitation, psychosis (sometimes with visual and tactile hallucinations), depressed mood, affect lability, mania, disorientation, libido changes

Nervous system disorders: headache, dizziness, tremor, dyskinesia including choreoathetoid movements, drowsiness, convulsions, cerebral arteritis and/or occlusion, serotonin syndrome in combination with serotonergic drugs, migraine, motor and verbal tics

Eye disorders: blurred vision, difficulties in visual accommodation, diplopia, mydriasis, increased intraocular pressure

Cardiac disorders: tachycardia, palpitations, increased blood pressure, arrhythmias, angina pectoris, sudden cardiac death, myocardial infarction, bradycardia, extrasystole

Respiratory, thoracic and mediastinal disorders: cough, pharyngolaryngeal pain, dyspnea

Gastrointestinal disorders: dry mouth, nausea, vomiting, abdominal pain, dyspepsia, diarrhea

General disorders: fatigue, hyperpyrexia

Hepatobiliary disorders: abnormal liver function, ranging from transaminase elevation to severe hepatic injury

Skin and subcutaneous tissue disorders: hyperhidrosis, pruritus, urticaria, exfoliative dermatitis, scalp hair loss, erythema multiforme rash, thrombocytopenic purpura, angioneurotic edema, erythema, fixed drug eruption

Musculoskeletal and connective tissue disorders: arthralgia, muscle cramps, rhabdomyolysis, myalgia, muscle twitching

Renal and urinary disorders: hematuria

Reproductive system and breast disorders: gynecomastia

Urogenital disorders: priapism

Vascular disorders: peripheral coldness, Raynaud’s phenomenon

Investigations: weight loss

7 DRUG INTERACTIONS

7.1 Clinically Important Drug Interactions

Table 1 presents clinically important drug interactions with methylphenidate hydrochloride.

Table 1: Drugs Having Clinically Important Interactions with methylphenidate hydrochloride
Monoamine Oxidase Inhibitors (MAOI)
Clinical Impact: | Concomitant use of MAOIs and CNS stimulants, including methylphenidate hydrochloride, can cause hypertensive crisis. Potential outcomes include death, stroke, myocardial infarction, aortic dissection, ophthalmological complications, eclampsia, pulmonary edema, and renal failure [see Contraindications (4)].
Intervention: | Concomitant use of methylphenidate hydrochloride with monoamine oxidase inhibitors (MAOIs) or within 14 days after discontinuing MAOI treatment is contraindicated.
Antihypertensive Drugs
Clinical Impact: | Methylphenidate hydrochloride may decrease the effectiveness of drugs used to treat hypertension [see Warnings and Precautions (5.3)].
Intervention: | Monitor blood pressure and adjust the dosage of the antihypertensive drug as needed.
Halogenated Anesthetics
Clinical Impact: | Concomitant use of halogenated anesthetics and methylphenidate hydrochloride may increase the risk of sudden blood pressure and heart rate increase during surgery.
Intervention: | Avoid use of methylphenidate hydrochloride in patients being treated with anesthetics on the day of surgery.
Risperidone
Clinical Impact: | Combined use of methylphenidate with risperidone when there is a change, whether an increase or decrease, in dosage of either or both medications, may increase the risk of extrapyramidal symptoms (EPS).
Intervention: | Monitor for signs of EPS.

8 USE IN SPECIFIC POPULATIONS

8.1 Pregnancy

Pregnancy Exposure Registry
There is a pregnancy exposure registry that monitors pregnancy outcomes in women exposed to ADHD medications, including methylphenidate hydrochloride, during pregnancy. Healthcare providers are encouraged to advise patients to register by calling the National Pregnancy Registry for ADHD Medications at 1-866-961-2388 or visiting online at www.womensmentalhealth.org/research/pregnancyregistry/adhd-medications/.

Risk Summary
Published studies and postmarketing reports on methylphenidate use during pregnancy have not identified a drug-associated risk of major birth defects, miscarriage or adverse maternal or fetal outcomes. There may be risks to the fetus associated with the use of CNS stimulants use during pregnancy (see Clinical Considerations).

No effects on morphological development were observed in embryo-fetal development studies with oral administration of methylphenidate to pregnant rats and rabbits during organogenesis at doses up to 12 and 19 times, respectively, the maximum recommended human dose (MRHD) of 60 mg/day given to adults on a mg/m^2 basis. However, spina bifida was observed in rabbits at a dose 65 times the MRHD given to adults. A decrease in pup body weight was observed in a pre- and post-natal development study with oral administration of methylphenidate to rats throughout pregnancy and lactation at doses 7 times the MRHD given to adults (see Data).

The estimated background risk of major birth defects and miscarriage for the indicated population is unknown. All pregnancies have a background risk of birth defect, loss, or other adverse outcomes. In the U.S. general population, the estimated background risk of major birth defects and miscarriage in clinically recognized pregnancies is 2% to 4% and 15% to 20%, respectively.

Clinical Considerations
Fetal/Neonatal Adverse Reactions
CNS stimulants, such as methylphenidate hydrochloride, can cause vasoconstriction and thereby decrease placental perfusion. No fetal and/or neonatal adverse reactions have been reported with the use of therapeutic doses of methylphenidate during pregnancy; however, premature delivery and low birth weight infants have been reported in amphetamine-dependent mothers.

Data
Animal Data
In embryo-fetal development studies conducted in rats and rabbits, methylphenidate was administered orally at doses of up to 75 and 200 mg/kg/day, respectively, during the period of organogenesis. Malformations (increased incidence of fetal spina bifida) were observed in rabbits at the highest dose, which is approximately 65 times the MRHD of 60 mg/day given to adults on a mg/m^2 basis. The no effect level for embryo-fetal development in rabbits was 60 mg/kg/day (19 times the MRHD given to adults on a mg/m^2 basis). There was no evidence of morphological development effects in rats, although increased incidences of fetal skeletal variations were seen at the highest dose level (12 times the MRHD of 60 mg/day given to adults on a mg/m^2 basis), which was also maternally toxic. The no effect level for embryo-fetal development in rats was 25 mg/kg/day (4 times the MRHD on a mg/m^2 basis). When methylphenidate was administered to rats throughout pregnancy and lactation at doses of up to 45 mg/kg/day, offspring body weight gain was decreased at the highest dose (7 times the MRHD of 60 mg/day given to adults on a mg/m^2 basis), but no other effects on postnatal development were observed. The no effect level for pre- and postnatal development in rats was 15 mg/kg/day (approximately 2 times the MRHD given to adults on a mg/m^2 basis).

8.2 Lactation

Risk Summary
Limited published literature, based on milk sampling from seven mothers reports that methylphenidate is present in human milk, which resulted in infant doses of 0.16% to 0.7% of the maternal weight-adjusted dosage and a milk/plasma ratio ranging between 1.1 and 2.7. There are no reports of adverse effects on the breastfed infant and no effects on milk production. Long-term neurodevelopmental effects on infants from stimulant exposure are unknown. The developmental and health benefits of breastfeeding should be considered along with the mother’s clinical need for methylphenidate hydrochloride and any potential adverse effects on the breastfed infant from methylphenidate hydrochloride or from the underlying maternal condition.

Clinical Considerations
Monitor breastfeeding infants for adverse reactions, such as agitation, insomnia, anorexia, and reduced weight gain.

8.4 Pediatric Use

The safety and effectiveness of methylphenidate hydrochloride for the treatment of ADHD have been established in pediatric patients six years of age and older. The safety and effectiveness of methylphenidate hydrochloride in pediatric patients under six years of age have not been established. The long-term efficacy of methylphenidate in pediatric patients has not been established.

Long-Term Suppression of Growth
Growth should be monitored during treatment with stimulants, including methylphenidate hydrochloride. Pediatric patients who are not growing or gaining weight as expected may need to have their treatment interrupted [see Warnings and Precautions (5.7), Adverse Reactions (6.1)].

Juvenile Animal Toxicity Data
In a study conducted in young rats, methylphenidate was administered orally at doses of up to 100 mg/kg/day for 9 weeks, starting early in the postnatal period (postnatal Day 7) and continuing through sexual maturity (postnatal Week 10). When these animals were tested as adults (postnatal Weeks 13 to 14), decreased spontaneous locomotor activity was observed in males and females previously treated with 50 mg/kg/day (approximately 4 times the MRHD of 60 mg/day given to children on a mg/m^2 basis) or greater, and a deficit in the acquisition of a specific learning task was seen in females exposed to the highest dose (8 times the MRHD given to children on a mg/m^2 basis). The no effect level for juvenile neurobehavioral development in rats (5 mg/kg/day) is less than the MRHD given to children on a mg/m^2 basis. The clinical significance of the long-term behavioral effects observed in rats is unknown.

8.5 Geriatric Use

Methylphenidate hydrochloride has not been studied in the geriatric population.

8.6 Renal Impairment

Methylphenidate hydrochloride has not been studied in patients with renal impairment.

9 DRUG ABUSE AND DEPENDENCE

9.1 Controlled Substance

Methylphenidate Hydrochloride Chewable Tablets contains methylphenidate, a Schedule II controlled substance.

9.2 Abuse

Methylphenidate hydrochloride has a high potential for abuse and misuse which can lead to the development of a substance use disorder, including addiction [see Warnings and Precautions (5.1)]. Methylphenidate hydrochloride can be diverted for non-medical use into illicit channels or distribution.

Abuse is the intentional, non-therapeutic use of a drug, even once, to achieve a desired psychological or physiological effect. Misuse is the intentional use, for therapeutic purposes, of a drug by an individual in a way other than prescribed by a healthcare provider or for whom it was not prescribed. Drug addiction is a cluster of behavioral, cognitive, and physiological phenomena that may include a strong desire to take the drug, difficulties in controlling drug use (e.g., continuing drug use despite harmful consequences, giving a higher priority to drug use than other activities and obligations), and possible tolerance or physical dependence.

Misuse and abuse of methylphenidate may cause increased heart rate, respiratory rate, or blood pressure; sweating; dilated pupils; hyperactivity; restlessness; insomnia; decreased appetite; loss of coordination; tremors; flushed skin; vomiting; and/or abdominal pain. Anxiety, psychosis, hostility, aggression, and suicidal or homicidal ideation have also been observed with CNS stimulants abuse and/or misuse. Misuse and abuse of CNS stimulants, including methylphenidate hydrochloride, can result in overdose and death [see Overdosage (10)], and this risk is increased with higher doses or unapproved methods of administration, such as snorting or injection.

9.3 Dependence

Physical Dependence

Methylphenidate hydrochloride may produce physical dependence. Physical dependence is a state that develops as a result of physiological adaptation in response to repeated drug use, manifested by withdrawal signs and symptoms after abrupt discontinuation or a significant dose reduction of a drug.

Withdrawal signs and symptoms after abrupt discontinuation or dose reduction following prolonged use of CNS stimulants including methylphenidate hydrochloride include dysphoric mood; depression; fatigue; vivid, unpleasant dreams; insomnia or hypersomnia; increased appetite; and psychomotor retardation or agitation.

Tolerance
Methylphenidate hydrochloride may produce tolerance. Tolerance is a physiological state characterized by a reduced response to a drug after repeated administration (i.e., a higher dose of a drug is required to produce the same effect that was once obtained at a lower dose).

10 OVERDOSAGE

Clinical Effects of Overdose

Overdose of CNS stimulants is characterized by the following sympathomimetic effects:

- Cardiovascular effects including tachyarrhythmias, and hypertension or hypotension. Vasospasm, myocardial infarction, or aortic dissection may precipitate sudden cardiac death. Takotsubo cardiomyopathy may develop.
- CNS effects including psychomotor agitation, confusion, and hallucinations. Serotonin syndrome, seizures, cerebral vascular accidents, and coma may occur.
- Life-threatening hyperthermia (temperatures greater than 104°F) and rhabdomyolysis may develop.

Overdose Management

Consider the possibility of multiple drug ingestion. Because methylphenidate has a large volume of distribution and is rapidly metabolized, dialysis is not useful. Consider contacting the Poison Help line (1-800-222-1222) or a medical toxicologist for additional overdose management recommendations.

11 DESCRIPTION

Methylphenidate hydrochloride is a mild central nervous system (CNS) stimulant, available as 2.5 mg, 5 mg and 10 mg chewable tablets for oral administration. methylphenidate hydrochloride is methyl α-phenyl-2-piperidineacetate hydrochloride, and its structural formula is

Methylphenidate hydrochloride USP is a white, odorless, fine crystalline powder. Its solutions are acid to litmus. It is freely soluble in water and in methanol, soluble in alcohol, and slightly soluble in chloroform and in acetone.

Each Methylphenidate Hydrochloride Chewable Tablet, for oral administration, contains 2.5 mg, 5 mg or 10 mg of methylphenidate hydrochloride USP. In addition, Methylphenidate Hydrochloride Chewable Tablets also contain the following inactive ingredients: microcrystalline cellulose, grape flavor, guar gum, maltose, stearic acid, and sucralose.

12 CLINICAL PHARMACOLOGY

12.1 Mechanism of Action

Methylphenidate Hydrochloride is a central nervous system (CNS) stimulant. The mode of therapeutic action in ADHD and narcolepsy is not known.

12.2 Pharmacodynamics

Methylphenidate is a racemic mixture comprised of the d- and l-threo enantiomers. The d-threo enantiomer is more pharmacologically active than the l-threo enantiomer. Methylphenidate blocks the reuptake of norepinephrine and dopamine into the presynaptic neuron and increases the release of these monoamines into the extraneuronal space.

Cardiac Electrophysiology
A formal QT study has not been conducted in subjects taking methylphenidate hydrochloride.

The effect of dexmethylphenidate, the pharmacologically active d-enantiomer of methylphenidate hydrochloride, on the QT interval was evaluated in a double-blind, placebo- and open-label active (moxifloxacin)-controlled study following single doses of 40 mg dexmethylphenidate hydrochloride extended-release capsule in 75 healthy volunteers. Electrocardiograms were collected up to 12 hours postdose. Frederica’s method for heart rate correction was employed to derive the corrected QT interval (QTcF). The maximum mean prolongation of QTcF intervals was less than 5 ms, and the upper limit of the 90% confidence interval was below 10 ms for all time-matched comparisons versus placebo. This was below the threshold of clinical concern and there was no evident exposure response relationship.

12.3 Pharmacokinetics

Absorption

Following oral administration of Methylphenidate Hydrochloride Chewable Tablets, peak plasma methylphenidate concentrations are achieved at about 1 to 2 hours. The mean Cmax following a 20 mg dose is approximately 10 ng/mL.

No clinically significant difference in methlyphenidate pharmacokinetics was observed between Methylphenidate Hydrochloride Chewable Tablets and immediate-release methylphenidate hydrochloride tablet.

Effect of Food
In a study in adult volunteers investigating the effects of a high-fat meal on the bioavailability of Methylphenidate Hydrochloride Chewable Tablets at a dose of 20 mg, the presence of food delayed the peak concentrations by approximately 1 hour (1.5 hours, fasted and 2.4 hours, fed). Overall, a high-fat meal increased the AUC of Methylphenidate Hydrochloride Chewable Tablets by about 20%, on average.

Distribution
Plasma protein binding is 10% to 33%. The volume of distribution was 2.65 ± 1.11 L/kg for d-methylphenidate and 1.80 ± 0.91 L/kg for l-methylphenidate.

Elimination
The mean terminal half-life (t½) of methylphenidate was 3 hours following administration of 20 mg Methylphenidate Hydrochloride Chewable Tablet. The systemic clearance is 0.40 ± 0.12 L/h/kg for d-methylphenidate and 0.73 ± 0.28 L/h/kg for l-methylphenidate.

Metabolism
In humans, methylphenidate is metabolized primarily via deesterification to alpha-phenylpiperidine acetic acid (PPA, ritalinic acid). The metabolite has little or no pharmacologic activity.

Excretion
After oral dosing of radiolabeled methylphenidate in humans, about 90% of the radioactivity was recovered in urine. The main urinary metabolite was PPA, accounting for approximately 80% of the dose.

The pharmacokinetics of the Methylphenidate Hydrochloride Chewable Tablets have been studied in healthy adult volunteers. The mean terminal half-life (t½) of methylphenidate following administration of 20 mg Methylphenidate Hydrochloride Chewable Tablets is 3 hours.

Specific Populations
Male and Female Patients, Racial Groups, and Age

The effect of gender, race, and age on the pharmacokinetics of methylphenidate after methylphenidate hydrochloride chewable tablets administration have not been studied.

Patients with Renal Impairment
There is no experience with the use of Methylphenidate Hydrochloride Chewable Tablets in patients with renal insufficiency. After oral administration of radiolabeled methylphenidate in humans, methylphenidate was extensively metabolized and approximately 80% of the radioactivity was excreted in the urine in the form of ritalinic acid. Since renal clearance is not an important route of methylphenidate clearance, renal insufficiency is expected to have little effect on the pharmacokinetics of Methylphenidate Hydrochloride Chewable Tablets.

Patients with Hepatic Impairment
There is no experience with the use of Methylphenidate Hydrochloride Chewable Tablets in patients with hepatic insufficiency.

13 NONCLINICAL TOXICOLOGY

13.1 Carcinogenesis, Mutagenesis, Impairment of Fertility

Carcinogenesis
In a lifetime carcinogenicity study carried out in B6C3F1 mice, methylphenidate caused an increase in hepatocellular adenomas and, in males only, an increase in hepatoblastomas, at a daily dose of approximately 60 mg/kg/day. This dose is approximately 5 times the maximum recommended human dose (MRHD) given to adults on a mg/m^2 basis. Hepatoblastoma is a relatively rare rodent malignant tumor type. There was no increase in total malignant hepatic tumors. The mouse strain used is sensitive to the development of hepatic tumors, and the significance of these results to humans is unknown.

Methylphenidate did not cause any increase in tumors in a lifetime carcinogenicity study carried out in F344 rats; the highest dose used was approximately 45 mg/kg/day, which is approximately 7 times the MRHD (adults) on a mg/m^2 basis.

In a 24-week carcinogenicity study in the transgenic mouse strain p53+/-, which is sensitive to genotoxic carcinogens, there was no evidence of carcinogenicity. Male and female mice were fed diets containing the same concentration of methylphenidate as in the lifetime carcinogenicity study; the high-dose groups were exposed to 60 to 74 mg/kg/day of methylphenidate.

Mutagenesis
Methylphenidate was not mutagenic in the in vitro Ames reverse mutation assay, in the in vitro mouse lymphoma cell forward mutation assay, or in the in vitro chromosomal aberration assay using human lymphocytes. Sister chromatid exchanges and chromosome aberrations were increased, indicative of a weak clastogenic response, in an in vitro assay in cultured Chinese Hamster Ovary (CHO) cells. Methylphenidate was negative in vivo in males and females in the mouse bone marrow micronucleus assay.

Impairment of Fertility
No human data on the effect of methylphenidate on fertility are available. Methylphenidate did not impair fertility in male or female mice that were fed diets containing the drug in an 18-week continuous breeding study. The study was conducted at doses up to 160 mg/kg/day, approximately 13 times the maximum recommended human dose of 60 mg/day given to adults on a mg/m^2 basis.

16 HOW SUPPLIED/STORAGE AND HANDLING

Each Methylphenidate Hydrochloride Chewable Tablet 2.5 mg is available as a white to off-white colored, grape flavored, rounded square shaped tablet with a convex surface, debossed with “τ” above “CHEW” on one side and “2.5” on the other side.

Bottles of 100 . . . . . . . . . NDC 64980-221-01

Each Methylphenidate Hydrochloride Chewable Tablet 5 mg is available as a white to off-white colored, grape flavored, rounded square shaped tablet with a convex surface, debossed with “τ” above “CHEW” on one side and “5” on the other side.

Bottles of 100 . . . . . . . . . NDC 64980-222-01

Each Methylphenidate Hydrochloride Chewable Tablet 10 mg is available as a white to off-white colored, grape flavored, scored rounded square shaped tablet with a convex surface, debossed with “τ” bisect “CHEW” on one side and “10” on the other side.

Bottles of 100 . . . . . . . . . NDC 64980-223-01

Protect from moisture. Dispense in tight container with child-resistant closure.

Storage: Store at 20° to 25°C (68° to 77°F) [see USP Controlled Room Temperature].

17 PATIENT COUNSELING INFORMATION

Advise the patient to read the FDA-approved patient labeling (Medication Guide).

Abuse, Misuse, and Addiction

Educate patients and their families about the risks of abuse, misuse, and addiction of methylphenidate hydrochloride, which can lead to overdose and death, and proper disposal of any unused drug [see Warnings and Precautions (5.1), Drug Abuse and Dependence (9.2), Overdosage (10)]. Advise patients to store methylphenidate hydrochloride in a safe place, preferably locked, and instruct patients to not give methylphenidate hydrochloride to anyone else.

Risks to Patients with Serious Cardiac Disease
Advise patients that there are potential risks to patients with serious cardiac disease, including sudden death with methylphenidate hydrochloride use. Instruct patients to contact a healthcare provider immediately if they develop symptoms such as exertional chest pain, unexplained syncope, or other symptoms suggestive of cardiac disease [see Warnings and Precautions (5.2)].

Increased Blood Pressure and Heart Rate
Advise patients and their caregivers that methylphenidate hydrochloride can cause elevations of their blood pressure and pulse rate [see Warnings and Precautions (5.3)].

Psychiatric Adverse Reactions
Advise patients and their caregivers that methylphenidate hydrochloride, at recommended doses, can cause psychotic or manic symptoms, even in patients without prior history of psychotic symptoms or mania [see Warnings and Precautions (5.4)].

Priapism
Advise patients, caregivers, and family members of the possibility of painful or prolonged penile erections (priapism). Instruct the patient to seek immediate medical attention in the event of priapism [see Warnings and Precautions (5.5)].

Circulation Problems in Fingers and Toes (Peripheral Vasculopathy, including Raynaud’s Phenomenon) [see Warnings and Precautions (5.6)]

- Instruct patients beginning treatment with methylphenidate hydrochloride about the risk of peripheral vasculopathy, including Raynaud’s phenomenon, and associated signs and symptoms: fingers or toes may feel numb, cool, painful, and/or may change color from pale, to blue, to red.
- Instruct patients to report to their healthcare provider any new numbness, pain, skin color change, or sensitivity to temperature in fingers or toes.
- Instruct patients to call their physician immediately with any signs of unexplained wounds appearing on fingers or toes while taking methylphenidate hydrochloride.
- Further clinical evaluation (e.g., rheumatology referral) may be appropriate for certain patients.

Long-Term Suppression of Growth in Pediatric Patients

Advise patients, families and caregivers that methylphenidate hydrochloride can cause slowing of growth and weight loss [see Warnings and Precautions (5.7)].

Increased Intraocular Pressure (IOP) and Glaucoma

Advise patients that IOP and glaucoma may occur during treatment with methylphenidate hydrochloride [see Warnings and Precautions (5.10)].

Motor and Verbal Tics, and Worsening of Tourette’s Syndrome

Advise patients that motor and verbal tics and worsening of Tourette’s syndrome may occur during treatment with methylphenidate hydrochloride. Instruct patients to notify their healthcare provider if emergence of new tics or worsening of tics or Tourette’s syndrome occurs [see Warnings and Precautions (5.11)].

Administration Information
Advise patients to take Methylphenidate Hydrochloride Chewable Tablets with at least 8 ounces (a full glass) of water or other fluid because the tablet may swell and block the throat or esophagus which may result in choking. Advise patients to discontinue Methylphenidate Hydrochloride Chewable Tablets and seek immediate medical attention if they experience chest pain, vomiting, difficulty in swallowing, or difficulty in breathing [see Dosage and Administration (2.2) and Warnings and Precautions (5.11)].

Pregnancy Registry
Advise patients that there is a pregnancy exposure registry that monitors pregnancy outcomes in women exposed to methylphenidate hydrochloride during pregnancy [see Use in Specific Populations (8.1)].

Manufactured for:
Rising Pharma Holdings, Inc.
East Brunswick, NJ 08816

Revised: 03/2025
PIR22301-05

MEDICATION GUIDE

(meth’’ il fen’ i date hye’’ droe klor’ ide)
Methylphenidate Hydrochloride Chewable Tablets CII

What is the most important information I should know about Methylphenidate Hydrochloride Chewable Tablets?

Methylphenidate Hydrochloride Chewable Tablets may cause serious side effects, including:

- Abuse, misuse, and addiction. Methylphenidate Hydrochloride Chewable Tablets has a high chance for abuse and misuse and may lead to substance use problems, including addiction. Misuse and abuse of Methylphenidate Hydrochloride Chewable Tablets, other methylphenidate containing medicines, and amphetamine containing medicines, can lead to overdose and death.

The risk of overdose and death is increased with higher doses of Methylphenidate Hydrochloride Chewable Tablets or when it is used in ways that are not approved, such as snorting or injection.

-
  - Your healthcare provider should check you or your child’s risk for abuse, misuse, and addiction before starting treatment with Methylphenidate Hydrochloride Chewable Tablets and will monitor you or your child during treatment.
  - Methylphenidate Hydrochloride Chewable Tablets may lead to physical dependence after prolonged use, even if taken as directed by your healthcare provider.
  - Do not give Methylphenidate Hydrochloride Chewable Tablets to anyone else. See “What is Methylphenidate Hydrochloride Chewable Tablets?” for more information.
  - Keep Methylphenidate Hydrochloride Chewable Tablets in a safe place and properly dispose of any unused medicine. See “How should I store Methylphenidate Hydrochloride Chewable Tablets?” for more information.
  - Tell your healthcare provider if you or your child have ever abused or been dependent on alcohol, prescription medicines, or street drugs.
- Risks for people with serious heart disease. Sudden death has happened in people who have heart defects or other serious heart disease.
  Your healthcare provider should check you or your child carefully for heart problems before starting and during treatment with Methylphenidate Hydrochloride Chewable Tablets. Tell your healthcare provider if you or your child have any heart problems, heart disease, or heart defects.
  Call your healthcare provider right away or go to the nearest hospital emergency room right away if you or your child have any signs of heart problems such as chest pain, shortness of breath, or fainting during treatment with Methylphenidate Hydrochloride Chewable Tablets.
  • Increased blood pressure and heart rate.
  Your healthcare provider should check you or your child’s blood pressure and heart rate regularly during treatment with Methylphenidate Hydrochloride Chewable Tablets.
  •Mental (psychiatric) problems, including:
  ° new or worse behavior or thought problems
  ° new or worse bipolar illness
  ° new psychotic symptoms (such as hearing voices, or seeing or believing things that are not real) or new manic symptoms
  Tell your healthcare provider about any mental problems you or your child have, or about a family history of suicide, bipolar illness, or depression.
  Call your healthcare provider right away if you or your child have any new or worsening mental symptoms or problems during treatment with Methylphenidate Hydrochloride Chewable Tablets, especially hearing voices, seeing or believing things that are not real, or new manic symptoms.

What is Methylphenidate Hydrochloride Chewable Tablets?
Methylphenidate Hydrochloride Chewable Tablets is a central nervous system (CNS) stimulant prescription medicine used for the treatment of:
• Attention Deficit Hyperactivity Disorder (ADHD) in people 6 years of age and older. Methylphenidate Hydrochloride Chewable Tablets may help increase attention and decrease impulsiveness and hyperactivity in people with ADHD.
• a sleep disorder called narcolepsy.

It is not known if Methylphenidate Hydrochloride Chewable Tablets is safe and effective in children under 6 years of age.
Methylphenidate Hydrochloride Chewable Tablets is a federally controlled substance (CII) because it contains methylphenidate that can be a target for people who abuse prescription medicines or street drugs. Keep Methylphenidate Hydrochloride Chewable Tablets in a safe place to protect it from theft. Never give your Methylphenidate Hydrochloride Chewable Tablets to anyone else, because it may cause death or harm them. Selling or giving away Methylphenidate Hydrochloride Chewable Tablets may harm others and is against the law.

Do not take Methylphenidate hydrochloride Chewable Tablets if you or your child:

- are allergic to methylphenidate or any of the ingredients in Methylphenidate Hydrochloride Chewable Tablets. See the end of this Medication Guide for a complete list of ingredients in Methylphenidate Hydrochloride Chewable Tablets.
- are taking, or have stopped taking within the past 14 days, a medicine called a monoamine oxidase inhibitor (MAOI).

Before taking Methylphenidate Hydrochloride Chewable Tablets tell your healthcare provider about all of your or your child’s medical conditions, including if you or your child:

- have heart problems, heart disease, heart defects, or high blood pressure
- have mental problems including psychosis, mania, bipolar illness, or depression, or have a family history of suicide, bipolar illness, or depression
- have circulation problems in fingers or toes
- have eye problems, including increased pressure in your eye, glaucoma, or problems with your close-up vision (farsightedness)
- have or had repeated movements or sounds (tics) or Tourette’s syndrome, or have a family history of tics or Tourette’s syndrome
- have trouble swallowing
- are pregnant or plan to become pregnant. It is not known if Methylphenidate Hydrochloride Chewable Tablets will harm your unborn baby.
  - There is a pregnancy registry for women who are exposed to Methylphenidate Hydrochloride Chewable Tablets during pregnancy. The purpose of the registry is to collect information about the health of women exposed to Methylphenidate Hydrochloride Chewable Tablets and their baby. If you or your child becomes pregnant during treatment with Methylphenidate Hydrochloride Chewable Tablets, talk to your healthcare provider about registering with the National Pregnancy Registry for ADHD Medications at 1-866-961-2388 or visit online at
    www.womensmentalhealth.org/research/pregnancyregistry/adhd-medications/.
- are breastfeeding or plan to breastfeed. Methylphenidate Hydrochloride passes into breast milk. Talk to your healthcare provider about the best way to feed the baby during treatment with Methylphenidate Hydrochloride Chewable Tablets.

Tell your healthcare provider about all of the medicines that you or your child take, including prescription and over-the-counter medicines, vitamins, and herbal supplements.
Methylphenidate Hydrochloride Chewable Tablets and some medicines may interact with each other and cause serious side effects. Sometimes the doses of other medicines will need to be changed during treatment with Methylphenidate Hydrochloride Chewable Tablets. Your healthcare provider will decide whether Methylphenidate Hydrochloride Chewable Tablets can be taken with other medicines.
Especially tell your healthcare provider if you or your child take an monoamine oxidase inhibitor (MAOI).
Know the medicines that you or your child take. Keep a list of your or your child’s medicines with you to show your or your child’s healthcare provider and pharmacist when you or your child get a new medicine. Do not start any new medicine during treatment with Methylphenidate Hydrochloride Chewable Tablets without talking to your or your child’s healthcare provider first.

How should I take Methylphenidate Hydrochloride Chewable Tablets?

- Take Methylphenidate Hydrochloride Chewable Tablets exactly as prescribed by your healthcare provider. Your healthcare provider may change the dose if needed.
- For children 6 years of age and older:
  - Take Methylphenidate Hydrochloride Chewable Tablets 2 times a day, 30 to 45 minutes before breakfast and lunch.
- For adults:
  - Take Methylphenidate Hydrochloride Chewable tablets 2 or 3 times a day, 30 to 45 minutes before a meal.
  - If you have trouble sleeping when Methylphenidate Hydrochloride Chewable Tablets is taken late in the day, take your last dose before 6 p.m.
- Chew Methylphenidate Hydrochloride Chewable Tablets well and swallow with at least 8 ounces (a full glass) of water or other liquid.
  ° Do not swallow Methylphenidate Hydrochloride Chewable Tablets whole.
  ° If you do not take enough liquid with Methylphenidate Hydrochloride Chewable Tablets, this can cause you to choke. Stop taking Methylphenidate Hydrochloride Chewable Tablets and get medical help right away if you or your child have chest pain, vomiting, trouble swallowing, or trouble breathing after taking Methylphenidate Hydrochloride Chewable Tablets.
- If you or your child takes too much Methylphenidate Hydrochloride Chewable Tablets, call your healthcare provider or Poison Help line at 1-800-222-1222 or go to the nearest hospital emergency room right away.

What are the possible side effects of Methylphenidate Hydrochloride Chewable Tablets?
Methylphenidate Hydrochloride Chewable Tablets may cause serious side effects, including:

- See “What is the most important information I should know about Methylphenidate Hydrochloride Chewable Tablets?”
- Painful and prolonged erections (priapism). Priapism that may require surgery has happened in males who take products that contain methylphenidate. If you or your child develops priapism, get medical help right away.
- Circulation problems in fingers and toes (peripheral vasculopathy, including Raynaud’s phenomenon). Signs and symptoms may include:
  - fingers or toes may feel numb, cool, or painful
  - fingers or toes may change color from pale, to blue, to red

Tell your healthcare provider if you or your child have numbness, pain, skin color change, or sensitivity to temperature in the fingers or toes or if you or your child have any signs of unexplained wounds appearing on fingers or toes during treatment with Methylphenidate Hydrochloride Chewable Tablets.

- Slowing of growth (height and weight) in children. Children should have their height and weight checked often during treatment with Methylphenidate Hydrochloride Chewable Tablets. Your healthcare provider may stop your child’s treatment with Methylphenidate Hydrochloride Chewable Tablets if your child is not growing or gaining weight as expected.
- Eye problems (increased pressure in the eye and glaucoma). Call your healthcare provider right away if you or your child develop changes in your vision or eye pain, swelling, or redness.
- New or worsening tics or worsening Tourette’s syndrome. Tell your healthcare provider if you or your child get any new or worsening tics or worsening Tourette’s syndrome during treatment with Methylphenidate Hydrochloride Chewable Tablets.

The most common side effects of Methylphenidate Hydrochloride Chewable Tablets include:

- increased heart rate
- irregular heart beat (palpitations)
- headache
- trouble sleeping
- anxiety
- sweating
- weight loss
- decreased appetite
- dry mouth
- nausea
- stomach (abdominal) pain

These are not all the possible side effects of Methylphenidate Hydrochloride Chewable Tablets.
Call your doctor for medical advice about side effects. You may report side effects to FDA at 1-800-FDA-1088.

How should I store Methylphenidate Hydrochloride Chewable Tablets?

- Store Methylphenidate Hydrochloride Chewable Tablets at room temperature between 68° to 77°F (20° to 25°C).
- Store Methylphenidate Hydrochloride Chewable Tablets in a safe place, like a locked cabinet.
- Protect Methylphenidate Hydrochloride Chewable Tablets from moisture.
- Dispose of remaining, unused, or expired Methylphenidate Hydrochloride Chewable Tablets by a medicine take-back program at a U.S. Drug Enforcement Administration (DEA) authorized collection site. If no take-back program or DEA authorized collector is available, mix Methylphenidate Hydrochloride Chewable Tablets with an undesirable, nontoxic substance such as dirt, cat litter, or used coffee grounds to make it less appealing to children and pets. Place the mixture in a container such as a sealed plastic bag and throw away Methylphenidate
  Hydrochloride Chewable Tablets in the household trash. Visit ww.fda.gov/drugdisposal for additional information on disposal of unused medicines.

Keep Methylphenidate Hydrochloride Chewable Tablets and all medicines out of the reach of children.

General information about the safe and effective use of Methylphenidate Hydrochloride Chewable Tablets.
Medicines are sometimes prescribed for purposes other than those listed in a Medication Guide. Do not use Methylphenidate Hydrochloride Chewable Tablets for a condition for which it was not prescribed. Do not give Methylphenidate Hydrochloride Chewable Tablets to other people, even if they have the same symptoms. It may harm them, and it is against the law. You can ask your pharmacist or healthcare provider for information about Methylphenidate Hydrochloride Chewable Tablets that is written for health professionals.

For more information, please contact Rising Pharma Holdings, Inc. at 1-844-874-7464.

What are the ingredients in Methylphenidate Hydrochloride Chewable Tablets?

Active Ingredient: methylphenidate hydrochloride USP

Inactive Ingredients: microcrystalline cellulose, grape flavor, guar gum, maltose, stearic acid, and sucralose.

This Medication Guide has been approved by the U.S. Food and Drug Administration.
Manufactured for:
Rising Pharma Holdings, Inc.
East Brunswick, NJ 08816

Revised: 03/2025
MGR22301-04

PRINCIPAL DISPLAY PANEL -5mg

NDC 64980-222-01
Methylphenidate Hydrochloride Chewable Tablets
5 mg
PHARMACIST: Please Dispense with Medication Guide provided with product.
100 Tablets
Rx only

PRINCIPAL DISPLAY PANEL - 2.5 mg

NDC 64980-221-01
Methylphenidate Hydrochloride Chewable Tablets
2.5 mg
PHARMACIST: Please Dispense with Medication Guide provided with product.
100 Tablets
Rx only

PRINCIPAL DISPLAY PANEL - 10 mg

NDC 64980-223-01
Methylphenidate Hydrochloride Chewable Tablets
10 mg
PHARMACIST: Please Dispense with Medication Guide provided with product.
100 Tablets
Rx only